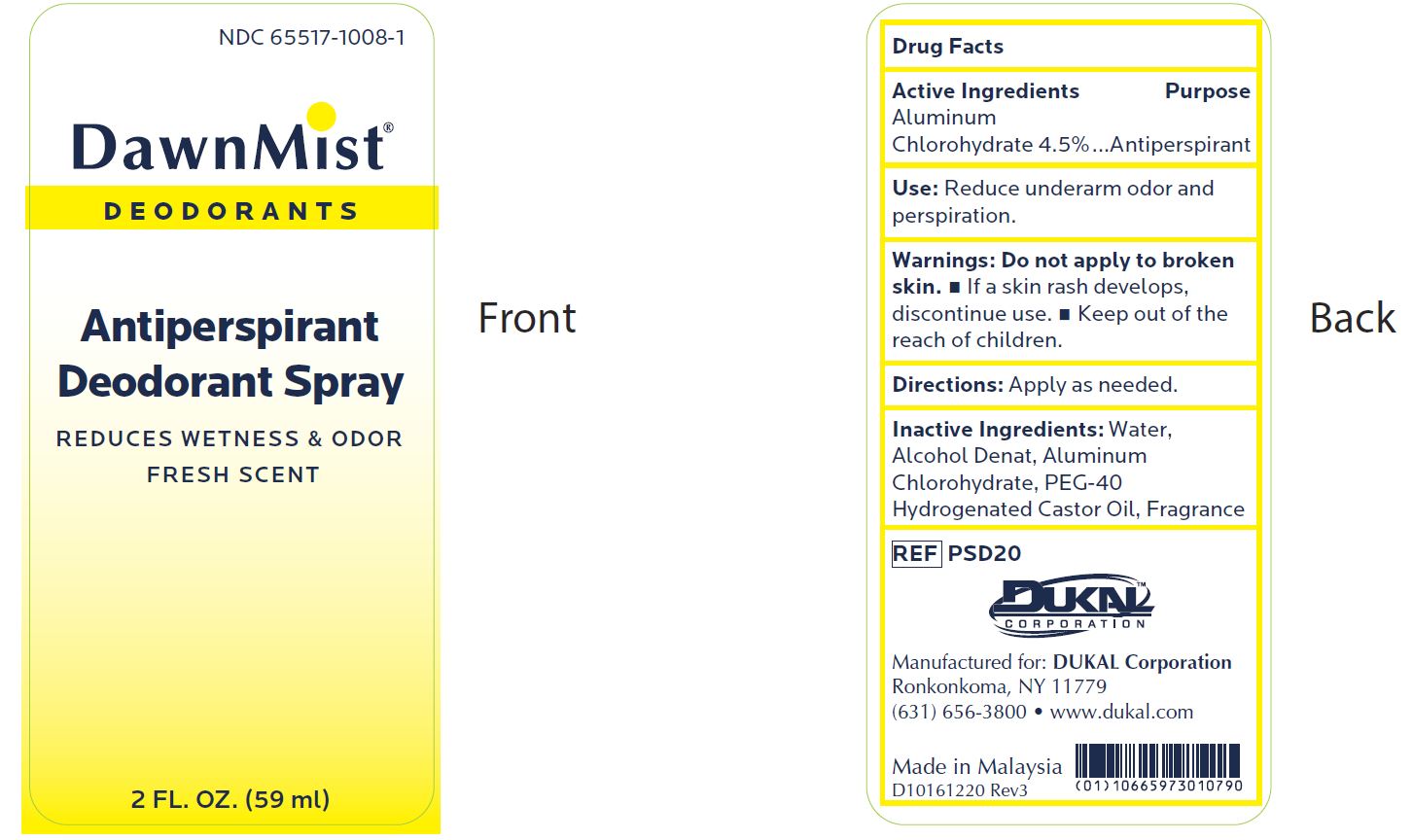 DRUG LABEL: DawnMist Antiperspirant Deodorant
NDC: 65517-1008 | Form: LIQUID
Manufacturer: Dukal LLC
Category: otc | Type: HUMAN OTC DRUG LABEL
Date: 20240723

ACTIVE INGREDIENTS: ALUMINUM CHLOROHYDRATE 45 mg/1 mL
INACTIVE INGREDIENTS: WATER; POLYOXYL 40 HYDROGENATED CASTOR OIL

DawnMist Antiperspirant Deodorant

Active Ingredient

Aluminum Chlorohydrate 4.5%

Purpose

Antiperspirant

Use

Reduces underarm perspiration.

Warnings

For external use only.

Do not use

on broken skin.

Discontinue use if

■irritation and redness
develop ■ If condition persists for more than 72
hours consult a doctor.

Ask a doctor before use

if you have kidney disease.

When using this product

■ Keep away from face and mouth ■ Do not spray near flames

Keep out of reach of children

■If swallowed, get medical help and contact Poison Control Center right away ■ Use only as directed

Directions

Apply to underarms only. Hold two inches from underarm and spray. Use daily for best results

Inactive Ingredients

Water, Alcohol Denat, PEG-40 Hydrogenated Castor Oil, Fragrance

Package Label

DawnMist

DEODERANTS

Antiperspirant Deodorant Spray

REDUCES WETNESS & ODOR

FRESH SCENTt

2 FL. OZ. (59ml)